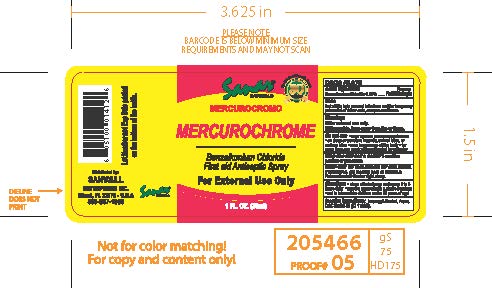 DRUG LABEL: Sanar Naturals Mercurochrome
NDC: 73386-146 | Form: SPRAY
Manufacturer: Sanvall Enterprises, Inc
Category: otc | Type: HUMAN OTC DRUG LABEL
Date: 20241031

ACTIVE INGREDIENTS: BENZALKONIUM CHLORIDE 0.26 mg/1 g
INACTIVE INGREDIENTS: WATER; ISOPROPYL ALCOHOL; D&C RED NO. 33

Sanar Naturals Mercurochrome

Active ingredient

Benzalkonium Chloride 0.26%

Purpose

First Aid Antiseptic

Uses

first aid to help prevent infections and for temporary pain relief of minor cuts, scrapes and burns

Warnings

For external use only

WHEN USING

Flammable, keep away from fire or flame

Keep out of reach of children.

If swallowed, get medical help or contact a Poison Control Center right away.

Stop use and ask a doctor if

condition persists or gets worse

Directions

- Clean affected area and spray 1 to 3 times daily
- May be covered with a sterile bandage
- Not to be used on children under 12 years of age

Inactive ingredients

Isopropyl Alcohol, Aqua, D&C Red #33 (CI 17200)